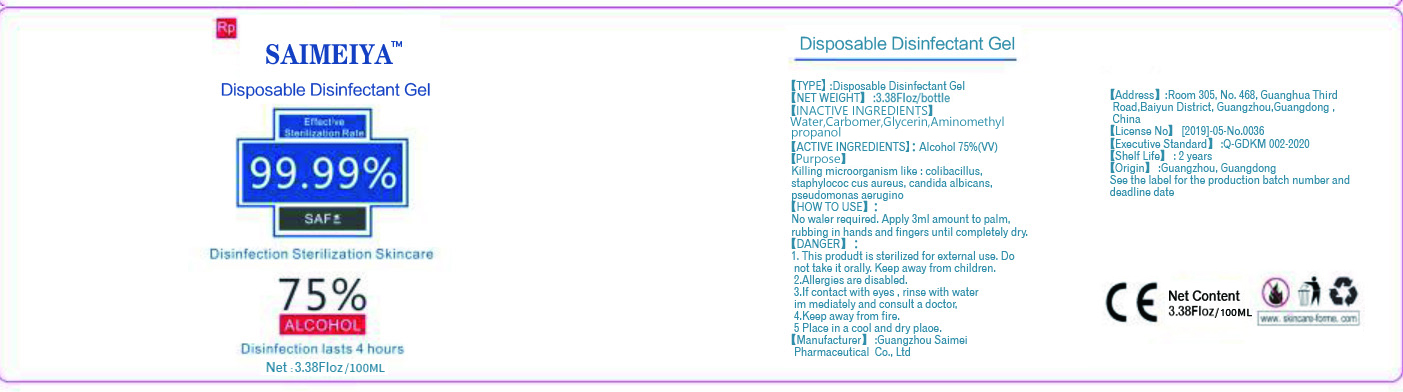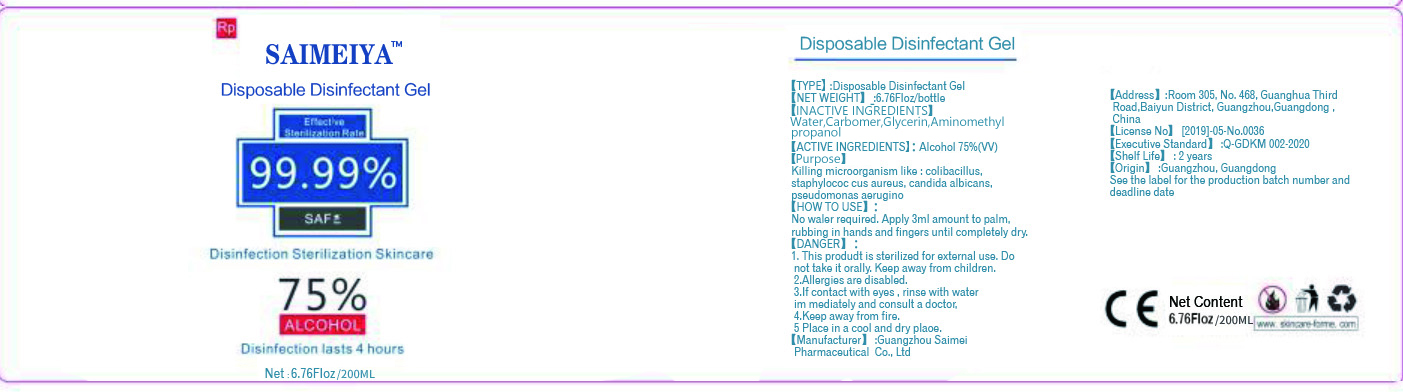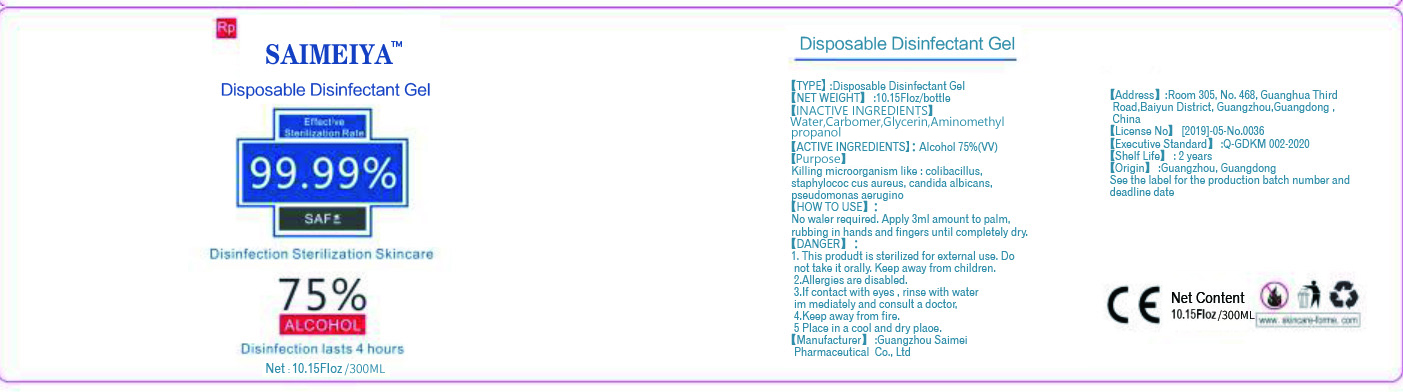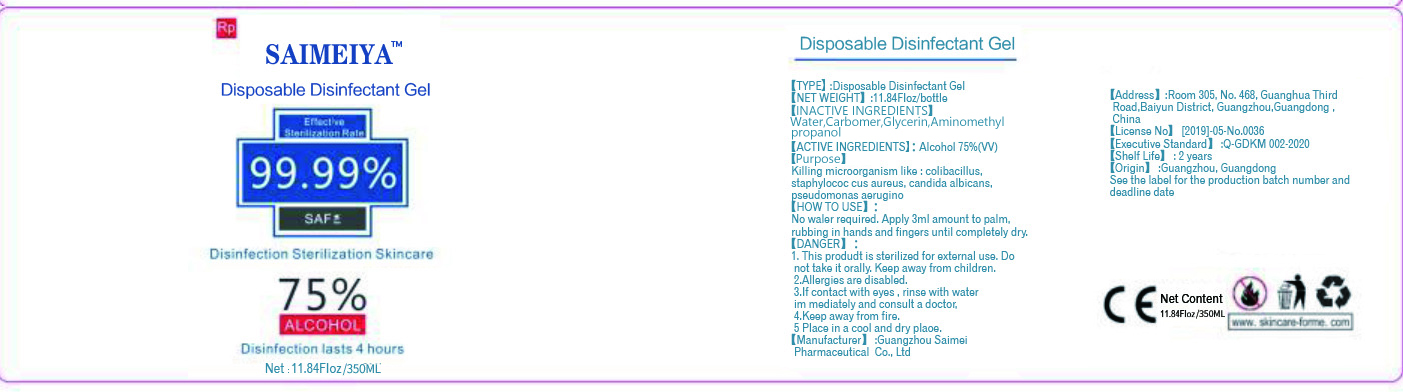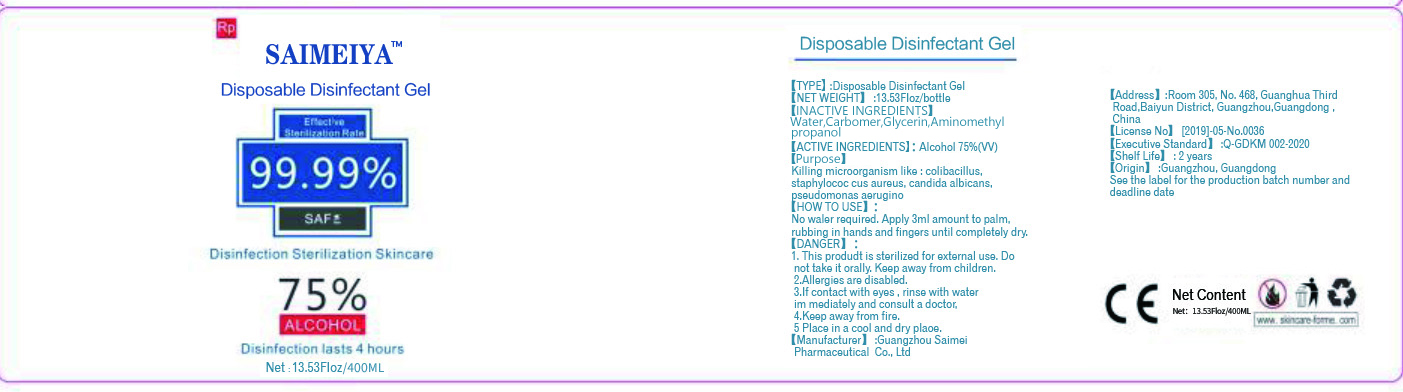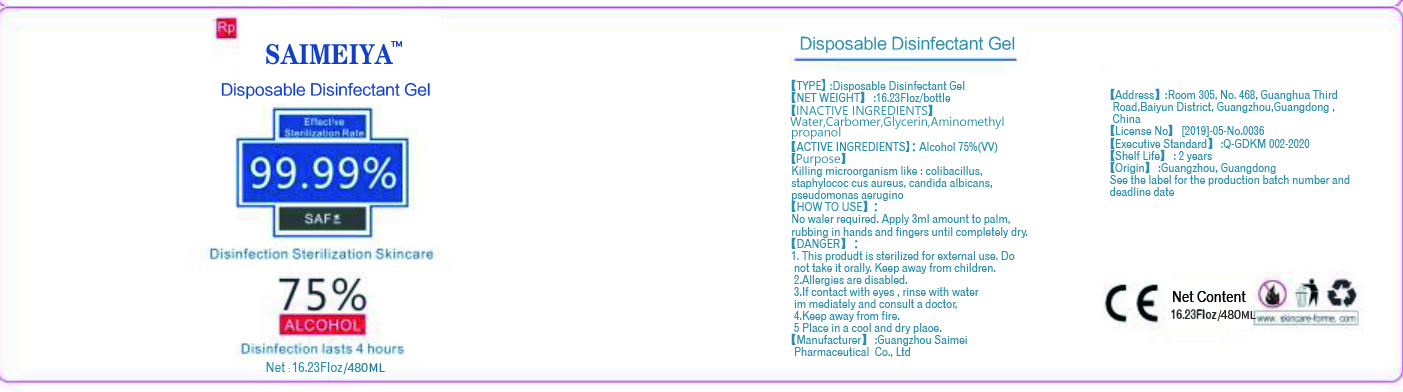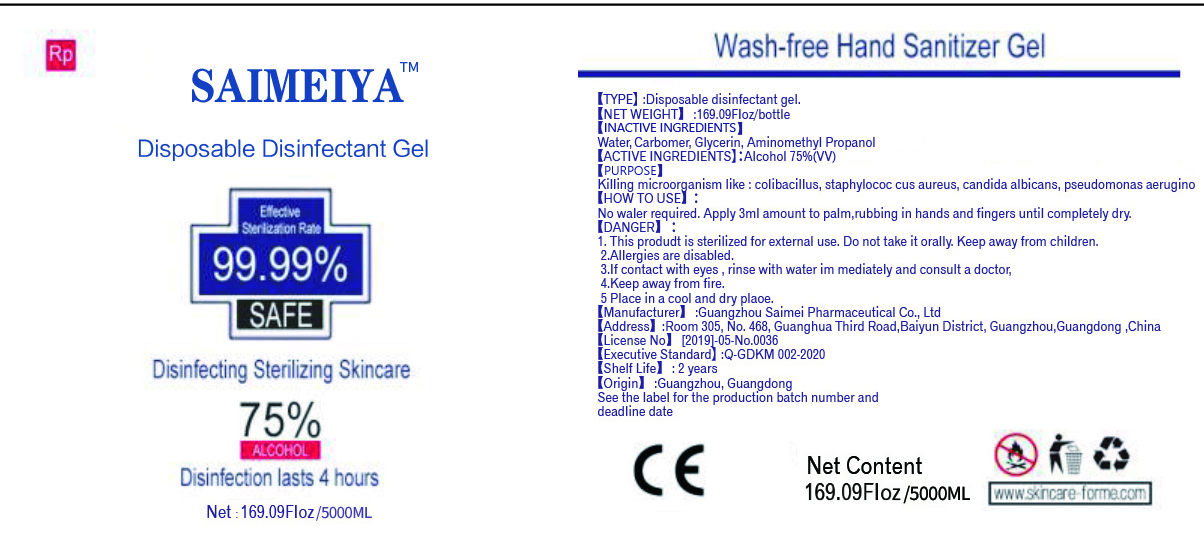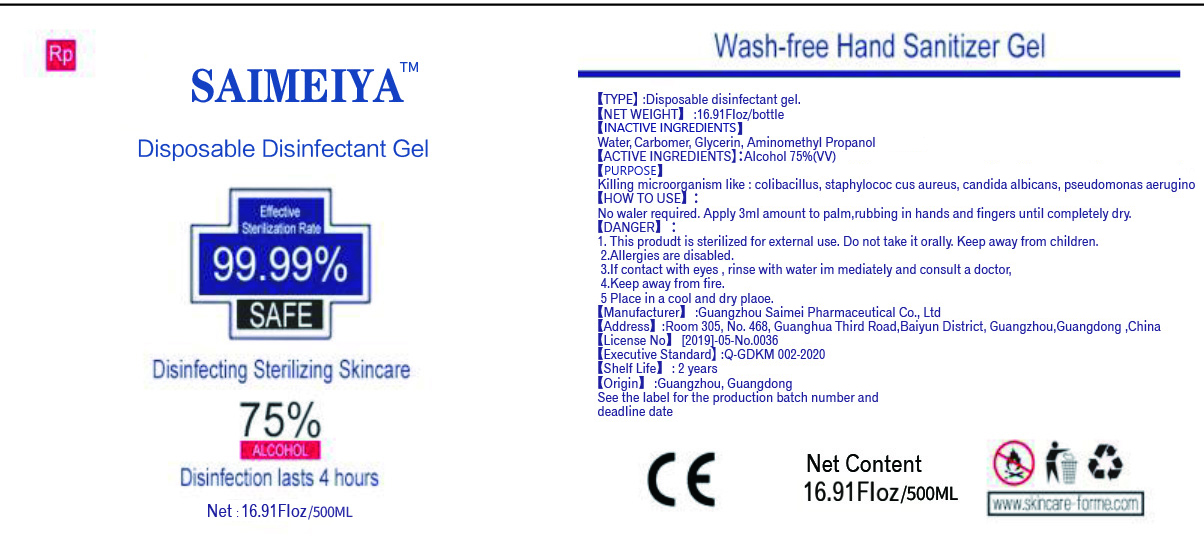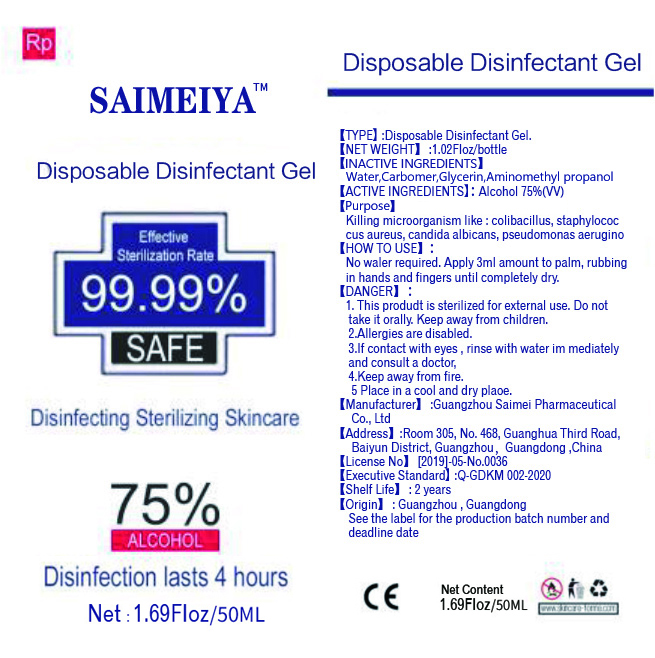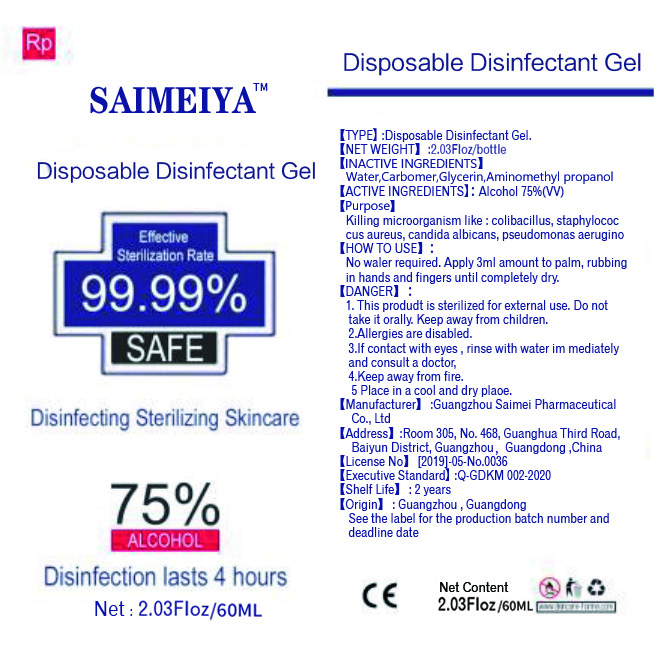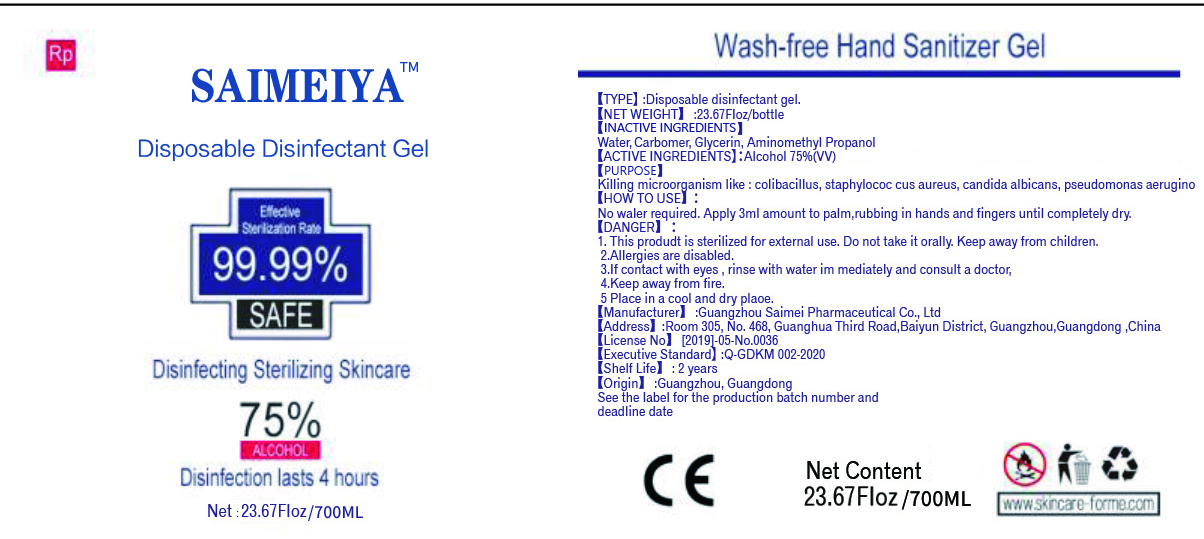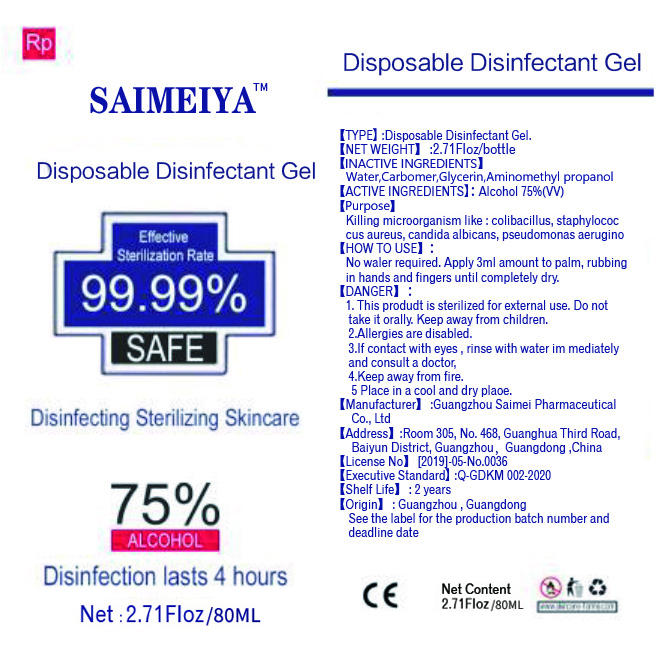 DRUG LABEL: Disposable disinfectant
NDC: 76680-007 | Form: GEL
Manufacturer: Guangzhou Saimei Pharmaceutical Co., Ltd
Category: otc | Type: HUMAN OTC DRUG LABEL
Date: 20200514

ACTIVE INGREDIENTS: ALCOHOL 75 mL/100 mL
INACTIVE INGREDIENTS: AMINOMETHYLPROPANOL 0.2 mL/100 mL; GLYCERIN 1.5 mL/100 mL; CARBOMER COPOLYMER TYPE C (ALLYL PENTAERYTHRITOL CROSSLINKED) 0.5 mL/100 mL; WATER 22.8 mL/100 mL

Disposable disinfectant gel

Active Ingredient(s)

Alcohol 75% v/v.

Purpose

Killing microorganism like: colibacillus, staphylococ cus aureus, candida albicans, pseudomonas aerugino

Use

No waler required. Apply 3 ml amount to palm, rubbing in hands and fingers until completely dry

Warnings

1. This produdt is sterilized for external use Do not take it orally. Keep away from children.
2. Allergies are disabled.
3. If contact with eyes, rinse with water im mediatelyand consult a doctor.
4. Keep away from fire.
5. Place in a cool and dry plaoe.

Do not use

This produdt is sterilized for external use Do not take it orally.

WHEN USING

Apply 3ml amount to palm, ubbing in hands and fingers until completely dry.

STOP USE

/

Keep out of reach of children.

Directions

/

Inactive ingredients

Water, Carbomer, Glycerin, Aminomethyl Propanol